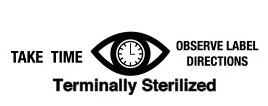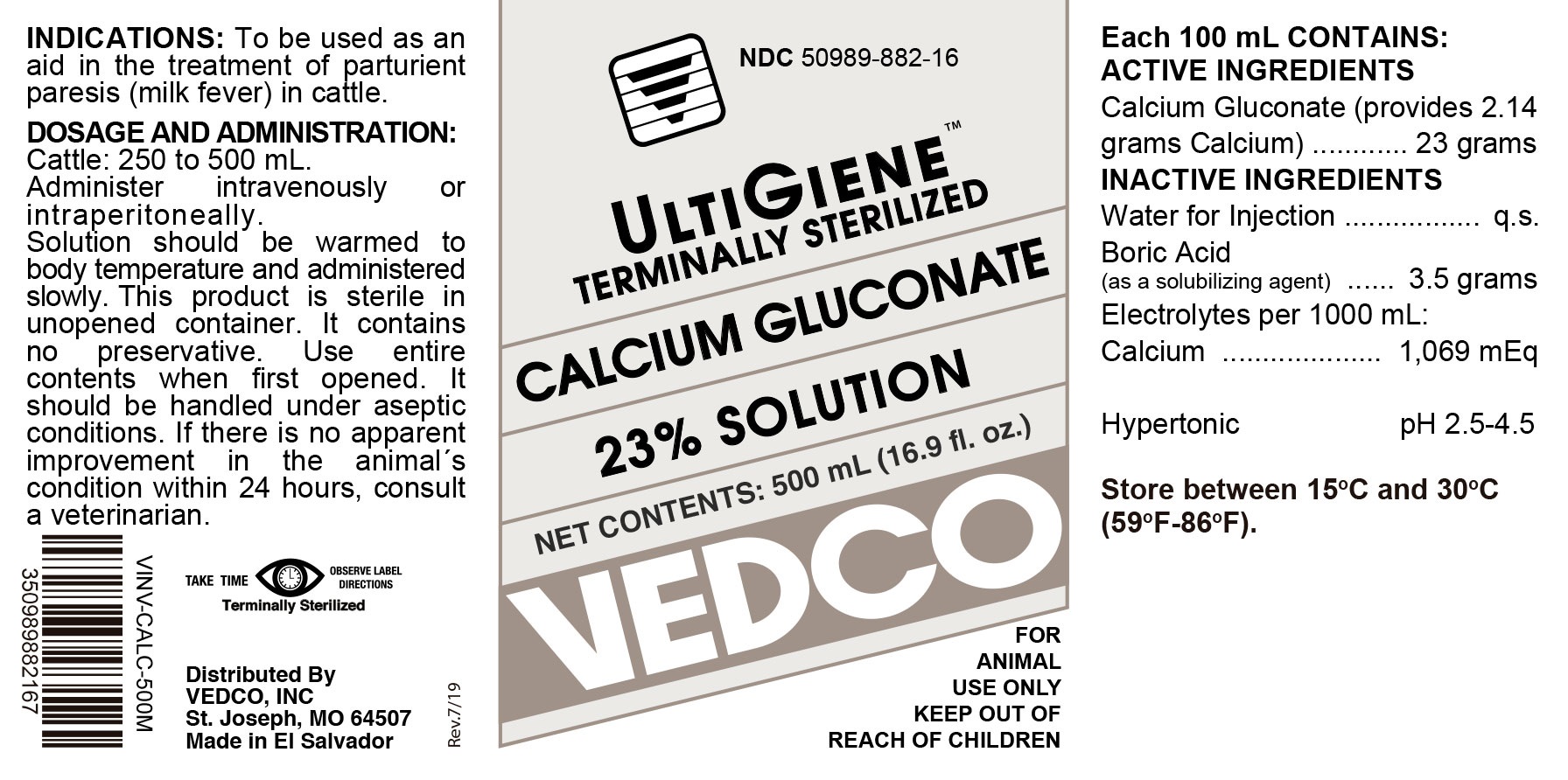 DRUG LABEL: Calcium Gluconate
NDC: 50989-882 | Form: INJECTION, SOLUTION
Manufacturer: Vedco
Category: animal | Type: OTC ANIMAL DRUG LABEL
Date: 20190822

ACTIVE INGREDIENTS: CALCIUM GLUCONATE 23 g/100 mL
INACTIVE INGREDIENTS: WATER; BORIC ACID 3.5 g/100 mL

CALCIUM GLUCONATE 23% SOLUTION

ACTIVE INGREDIENTS:

Each 100 mL contains:

Calcium Gluconate ................. 23 grams

(provides 2.14 grams Calcium)

Electrolytes per 1000 mL:

Calcium ......................... 1,069 mEq

Hypertonic pH 2.5-4.5

INACTIVE INGREDIENTS

Water for Injection ............ qs

Boric Acid .......................... 3.5 grams

INDICATIONS

To be used as an aid in treatment of parturient paresis (milk fever) in cattle

DOSAGE AND ADMINISTRATION:

Cattle: 200 to 500 mL.

Administer intravnously or intraperitoneally.

Solution should be warmed to body temperature and administered slowly. This product is sterile in unopened container. It contains no preservative. Use entire content when first opened. It should be handled under aseptic conditions. If there is no apparent improvement in animal's conditionwithin 24 hours, consult a veterinarian.

STORAGE

Store at 15oC to 30oC (59oF - 86oF).

KEEP OUT OF REACH OF CHILDREN

VETERINARY INDICATIONS

FOR ANIMAL USE ONLY

SAFE HANDLING WARNING

TAKE TIME OBSERVE LABEL DIRECTIONS

Termnally Sterilized

Distributed By

VEDCO, INC.

St. Joseph, MO 64507

Made in El Salvador

PRINCIPAL DISPLAY PANEL

NDC 50989-882-16

ULTIGIENETM TERMINALLY STERILIZED

CALCIUM GLUCONATE 23% SOLUTION

NET CONTENTS: 500 mL (16.9 f. oz.)

VEDCO

FOR ANIMAL USE ONLY

KEEP OUT OF REACH OF CHILDREN